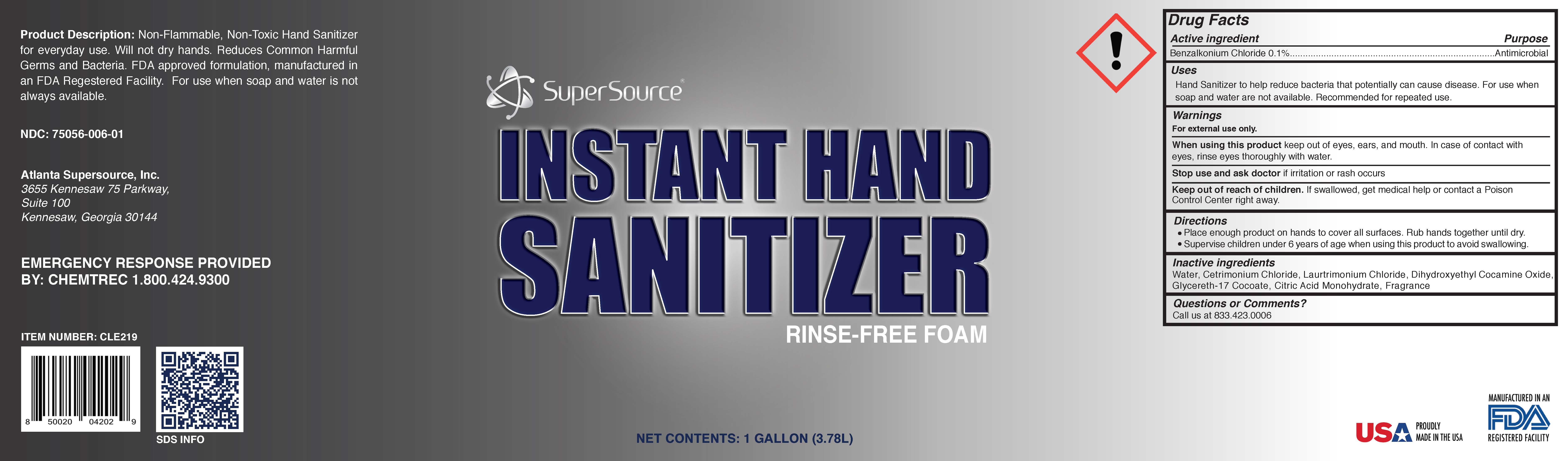 DRUG LABEL: Hand Sanitizer
NDC: 75056-006 | Form: AEROSOL, FOAM
Manufacturer: Atlanta Supersource, Inc.
Category: otc | Type: HUMAN OTC DRUG LABEL
Date: 20221205

ACTIVE INGREDIENTS: BENZALKONIUM CHLORIDE 0.1 g/100 g
INACTIVE INGREDIENTS: DIHYDROXYETHYL COCAMINE OXIDE 0.0099 g/100 g; CETRIMONIUM CHLORIDE 0.0099 g/100 g; WATER 99.8703 g/100 g; LAURTRIMONIUM CHLORIDE 0.0099 g/100 g

SS Hand Sanitizer Foam - BAC

Hand Sanitizer Foam BAC

Product Description: Non-Flammable, Non-Toxic Hand Sanitizer for everyday use. Will not dry hands. Reduces Common Harmful Germs and Bacteris. FDA approved formulation, manufactured in an FDA Registered Facility. For use when soap and water is not always available.

NDC: 75056-006-01

Atlanta Supersource, Inc.

3655 Kennesaw 75 Parkway

Suite 100

Kennesaw, Georgia 30144

EMERGENCY RESPONSE PROVIDED BY: Chemtrec 1.800.424.9300

Item Number: CLE219

Proudly Made in the USA

Manufactured in an FDA Registered Facility

Active Ingredient (s)

Benzalkonium Chloride 0.1%

Purpose

Antimicrobial

Uses

Hand Sanitizer to help reduce bacteria that can potntially cause disease. For use when soap and water are not available. Recommended for repeated use.

Warnings

For external use only.

When using this product

keep out of eyes, ears, and mouth. In case of contact with eyes, rinse eyes thouroughly with water.

Stop use and ask doctor

if irritation or rash occurs.

Keep out of reach of children. If swallowed, get medical help or contact a Poison Control Center right away.

Directions

Place enough product on hands to cover all surfaces. Rub hands together until dry. Supervise children under 6 years of age when using this product to avoid swallowing.

Inactive Ingredients

Water, Laurtrimonium Chloride, Cetrimonium Chloride, Dihydroxyethyl Cocamine Oxide

Glycereth-17 Cocoate, Citric Acid Monohydrate - these are not on the Product Data Sheet and Katie explained they do not need to be listed.

Questions or Comments?

Call us at 833.423.0006

Supersource Instant Hand Sanitizer Rinse-Free Foam

Net Contents: 1 Gallon (3.78L)